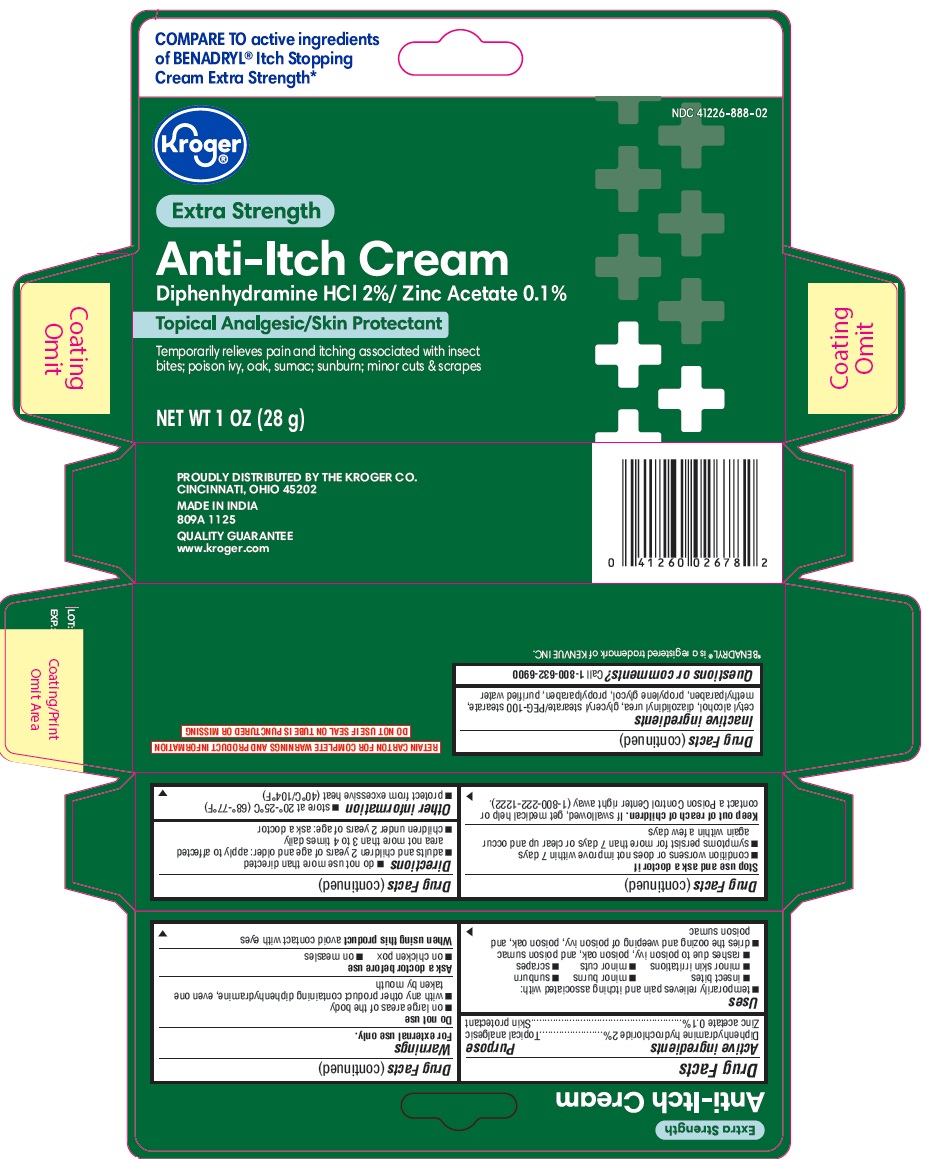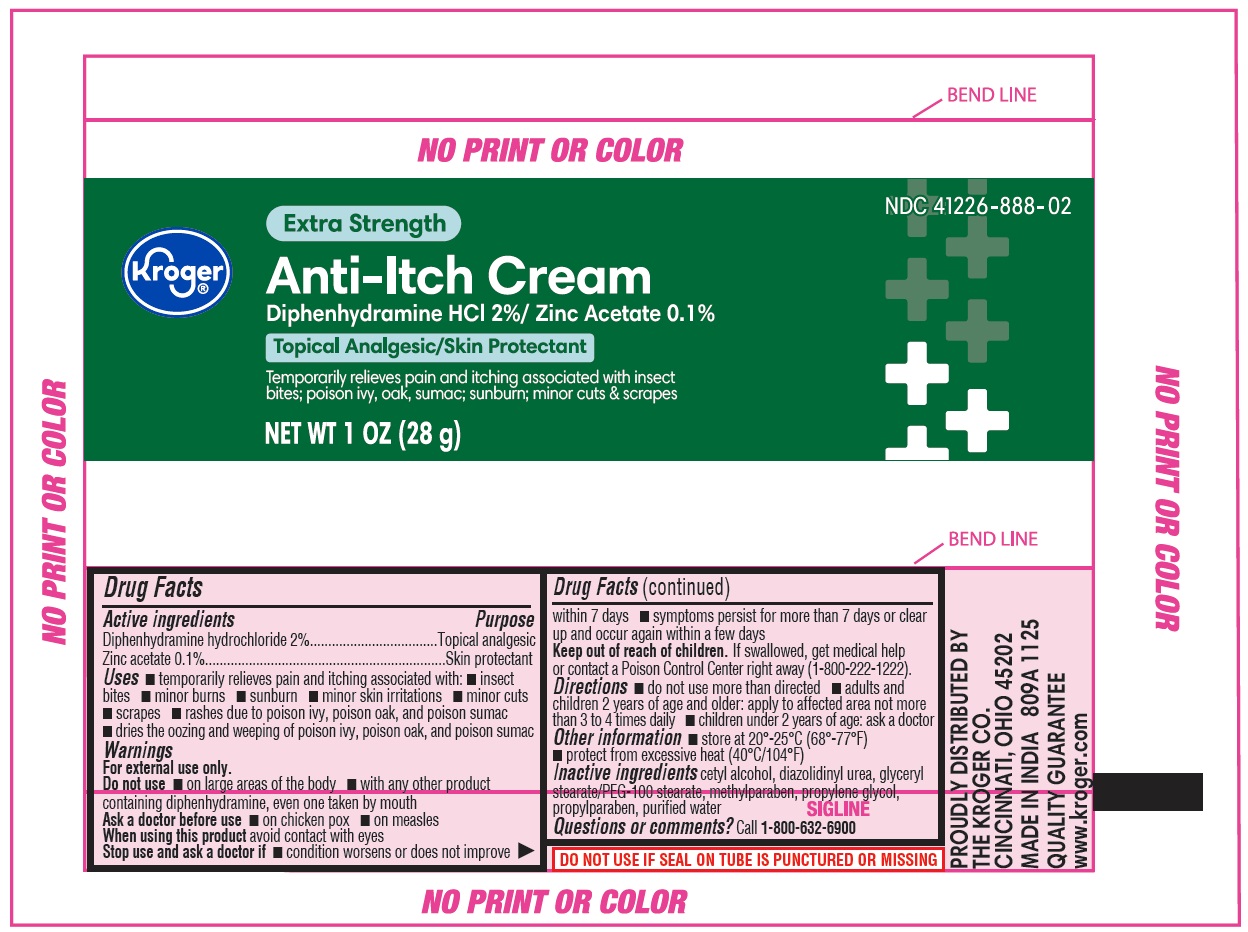 DRUG LABEL: Anti-Itch Cream
NDC: 41226-888 | Form: CREAM
Manufacturer: Kroger
Category: otc | Type: HUMAN OTC DRUG LABEL
Date: 20251113

ACTIVE INGREDIENTS: ZINC ACETATE 1 mg/1 g; DIPHENHYDRAMINE HYDROCHLORIDE 20 mg/1 g
INACTIVE INGREDIENTS: PROPYLPARABEN; CETYL ALCOHOL; DIAZOLIDINYL UREA; METHYLPARABEN; WATER; GLYCERYL STEARATE/PEG-100 STEARATE; PROPYLENE GLYCOL

Kroger Anti-Itch Cream

Drug Facts

-

Active ingredients

Diphenhydramine hydrochloride 2%

Zinc acetate 0.1%

Purpose

Topical analgesic

Skin protectant

Uses

-temporarily relieves pain and itching associated with:

- insect bites
- minor burns
- sunburn
- minor skin irritations
- minor cuts
- scrapes
- rashes due to poison ivy, poison oak, and poison sumac

-dries the oozing and weeping of poison ivy, poison oak, and poison sumac

Warnings

For external use only.

Do not use

- on large areas of the body
- with any other product containing diphenhydramine, even one taken by mouth

Ask a doctor before use

- on chicken pox
- on measles

When using this product

avoid contact with eyes

Stop use and ask a doctor if

- condition worsens or does not improve within 7 days
- symptoms persist for more than 7 days or clear up and occur again within a few days

Keep out of reach of children.

If swallowed, get medical help or contact a Poison Control Center right away (1-800-222-1222).

Directions

- do not use more than directed
- adults and children 2 years of age and older: apply to affected area not more than 3 to 4 times daily
- children under 2 years of age: ask a doctor

Other information

- store at 20° - 25°C (68°-77°F)
- protect from excessive heat (40°C/104°F)

Inactive ingredients

cetyl alcohol, diazolidinyl urea, glyceryl stearate/PEG-100 stearate, methylparaben, propylene glycol, propylparaben, purified water

Questions or comments?

Call 1-800-632-6900